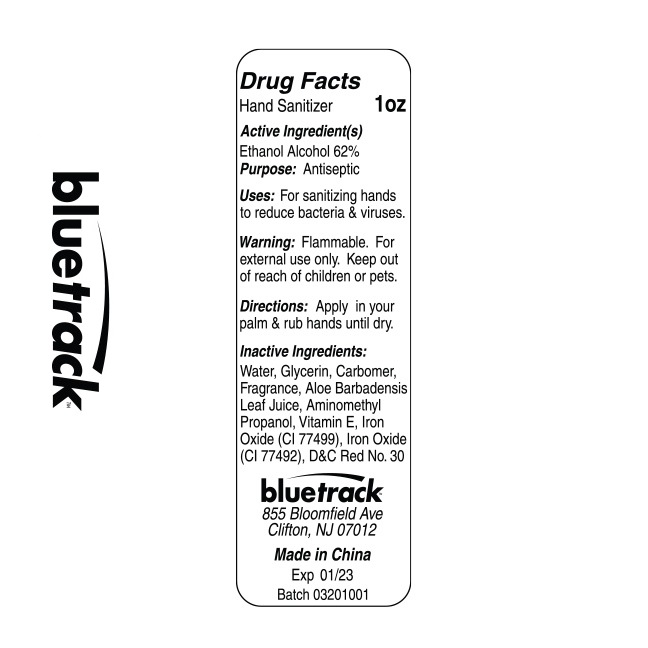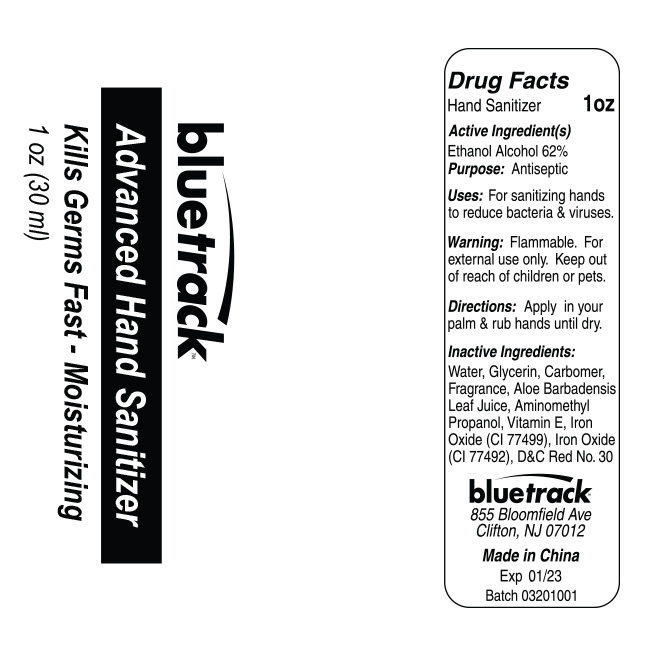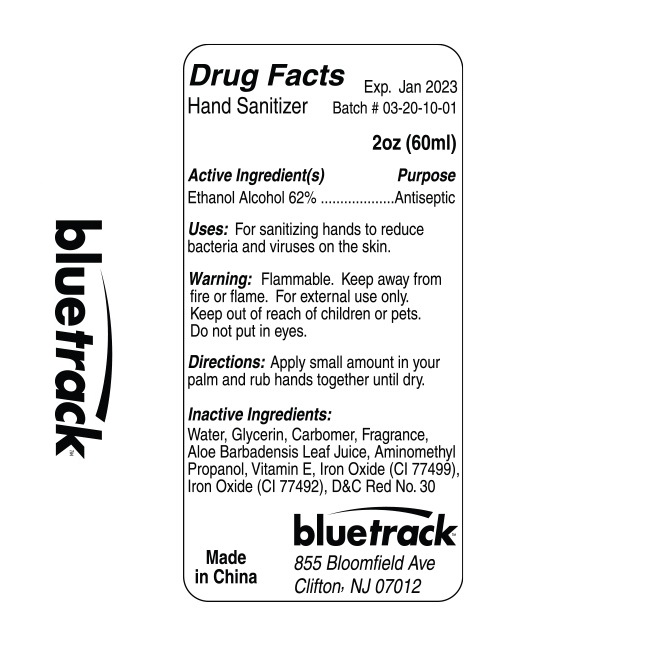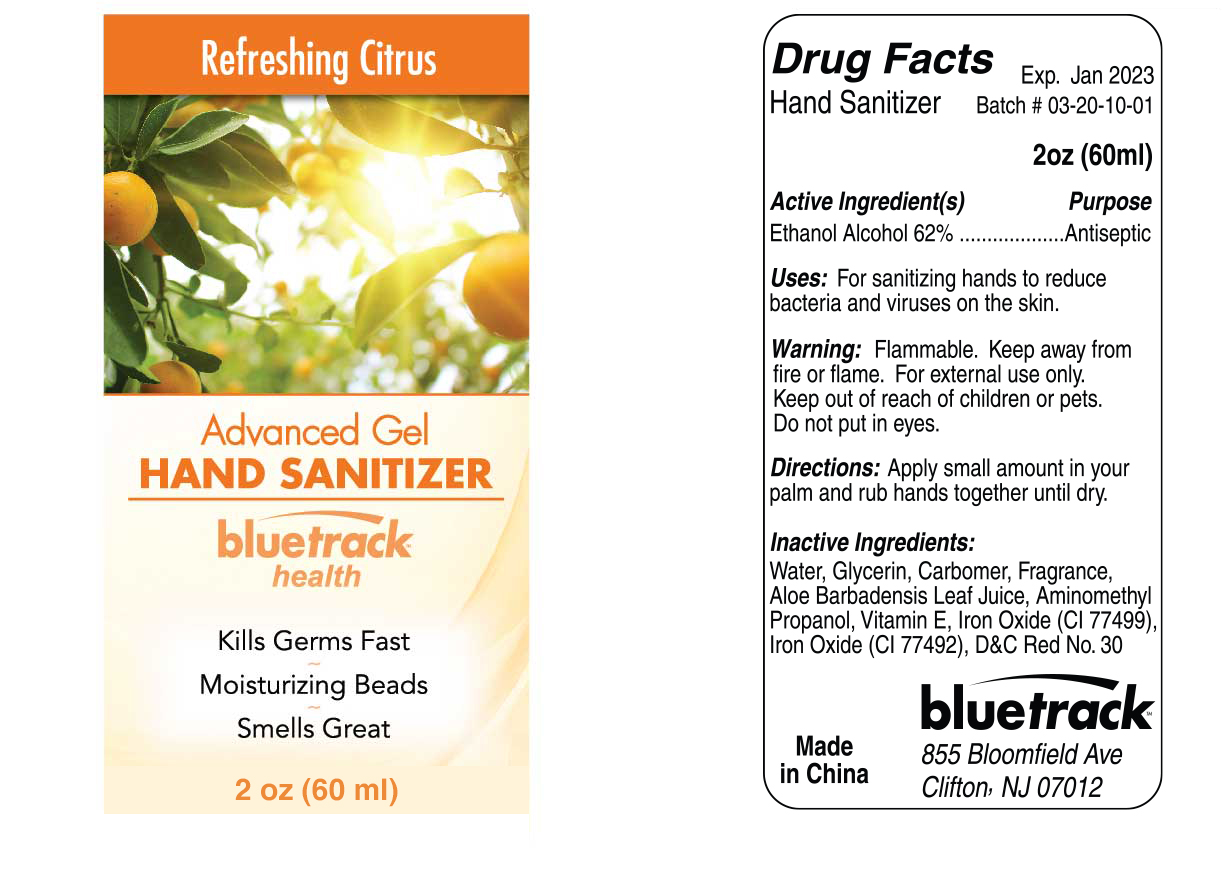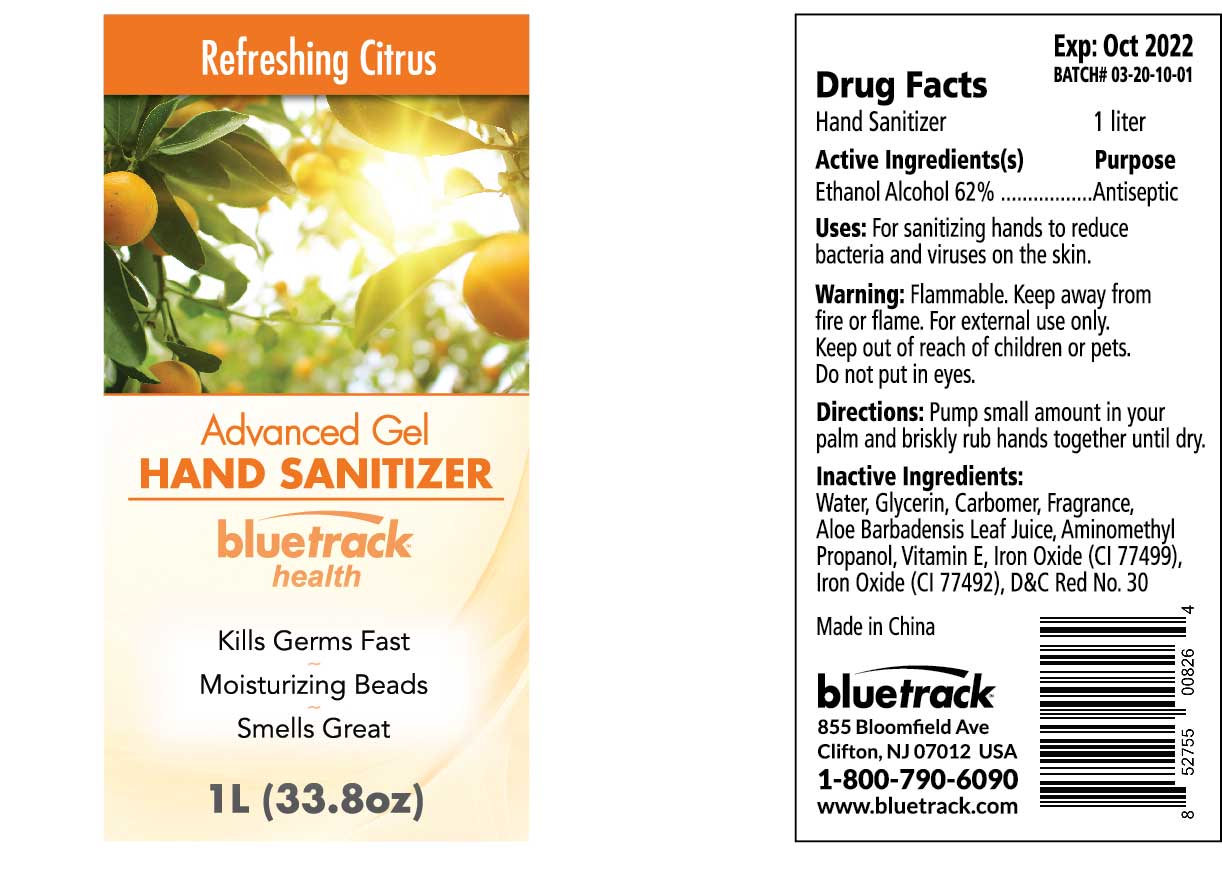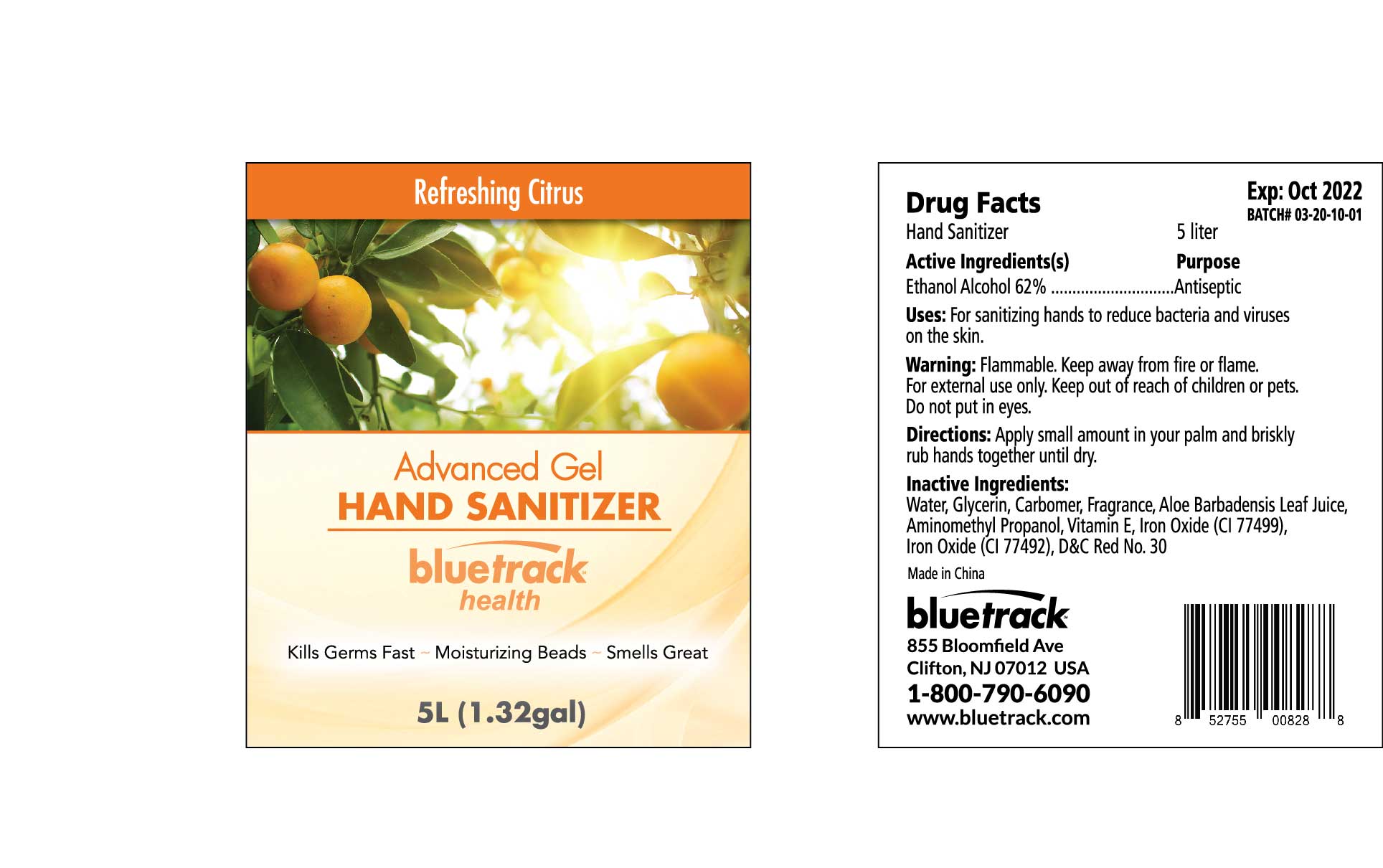 DRUG LABEL: Advanced Gel Hand Sanitizer Refreshing Citrus
NDC: 81209-100 | Form: GEL
Manufacturer: BLUETRACK, Inc.
Category: otc | Type: HUMAN OTC DRUG LABEL
Date: 20210803

ACTIVE INGREDIENTS: ALCOHOL 62 mL/100 mL
INACTIVE INGREDIENTS: ALOE VERA LEAF; FRAGRANCE FRESH CITRUS FLORAL ORC1501495; TOCOPHEROL; FERROSOFERRIC OXIDE; FERRIC OXIDE YELLOW; D&C RED NO. 30; AMINOMETHYLPROPANOL; GLYCERIN; CARBOMER 940; WATER

Advanced Gel HAND SANITIZER Refreshing Citrus

Active Ingredient(s)

Ethanol Alcohol 62% . Purpose: Antiseptic

Purpose

Antiseptic, Hand Sanitizer

Use

For Sanitizing hands to reduce bacteria and virus on the skin

Warnings

Flammable. Keep away from fire or flame

For external use only.

Keep out of reach of childrens or pets.

WHEN USING

Do not put in eyes

Directions

Apply Small amount in your palm and briskly rub hands together until dry.

Inactive ingredients

Water, Glycerin, Carbomer, Fragrance, Aloe Barbadensis Leaf Juice, Aminomethyl Propanol, Vitamin E, Iron Oxide(CI 77499),Iron Oxide(CI 77492), D&C Red No.30.

Package Label - Principal Display Panel

5000 mL NDC: 81209-100-01

1000mL NDC: 81209-100-02

30mL NDC :81209-100-03

30mL promotional NDC :81209-100-04

60mL NDC :81209-100-05

60mL Promotional NDC 81209-100-06